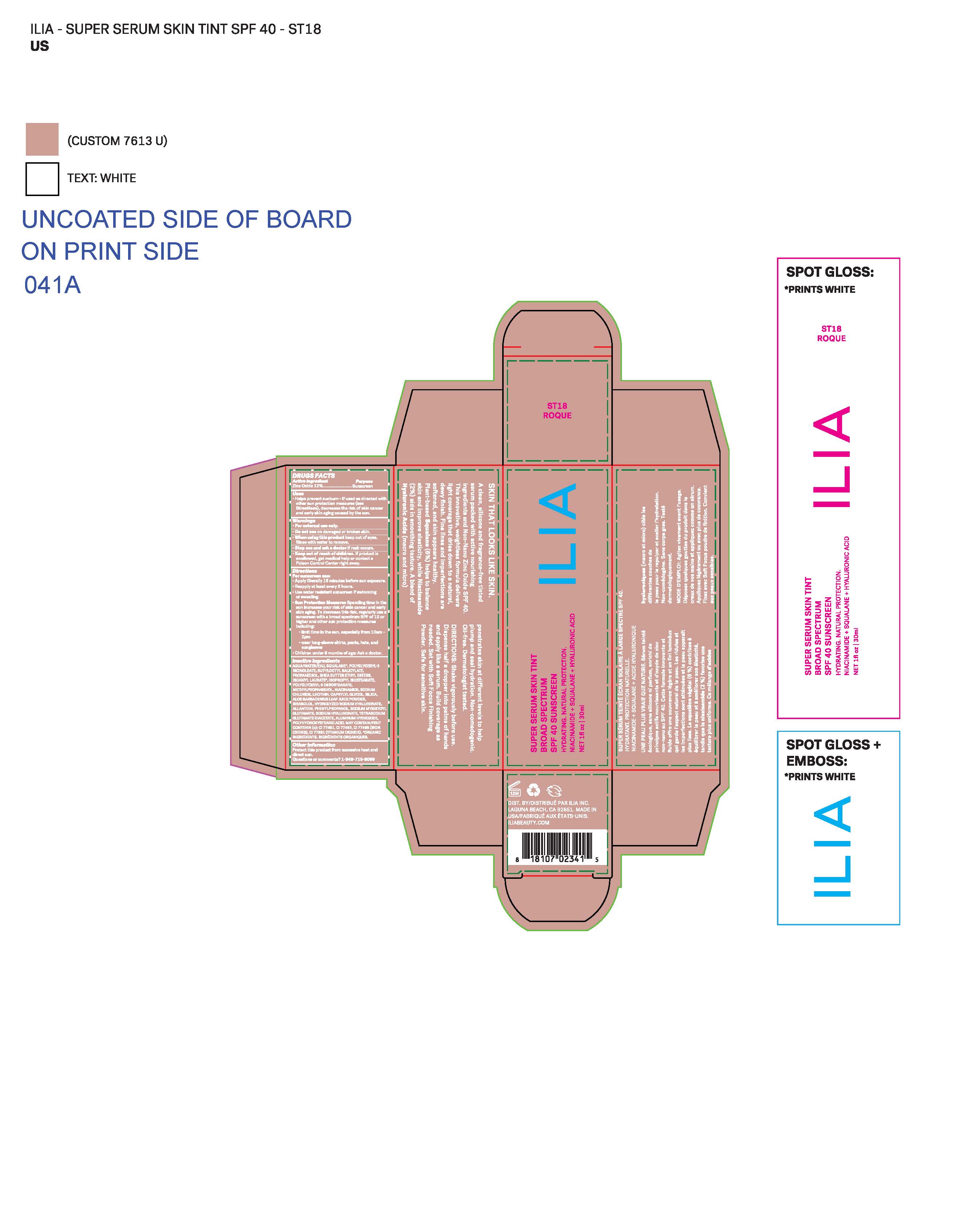 DRUG LABEL: ILIA SUPER SERUM SKIN TINT (ST18 MALI)
NDC: 81110-766 | Form: LOTION
Manufacturer: Ilia, Inc.
Category: otc | Type: HUMAN OTC DRUG LABEL
Date: 20251030

ACTIVE INGREDIENTS: ZINC OXIDE 132 mg/1 mL
INACTIVE INGREDIENTS: ALLANTOIN; SILICON DIOXIDE; SQUALANE; BUTYLOCTYL SALICYLATE; HYALURONATE SODIUM; ALOE VERA LEAF; TITANIUM DIOXIDE; SODIUM MYRISTOYL GLUTAMATE; ALUMINUM HYDROXIDE; WATER; NIACINAMIDE; PROPANEDIOL; SODIUM CHLORIDE; PHENYLPROPANOL; METHYLPROPANEDIOL; SHEA BUTTER; ISOAMYL LAURATE; POLYGLYCERYL-3 DIISOSTEARATE; ISOPROPYL ISOSTEARATE; .ALPHA.-BISABOLOL, (+)-; CAPRYLYL GLYCOL; LECITHIN, SOYBEAN

ILIA SUPER SERUM SKIN TINT (ST18 MALI)